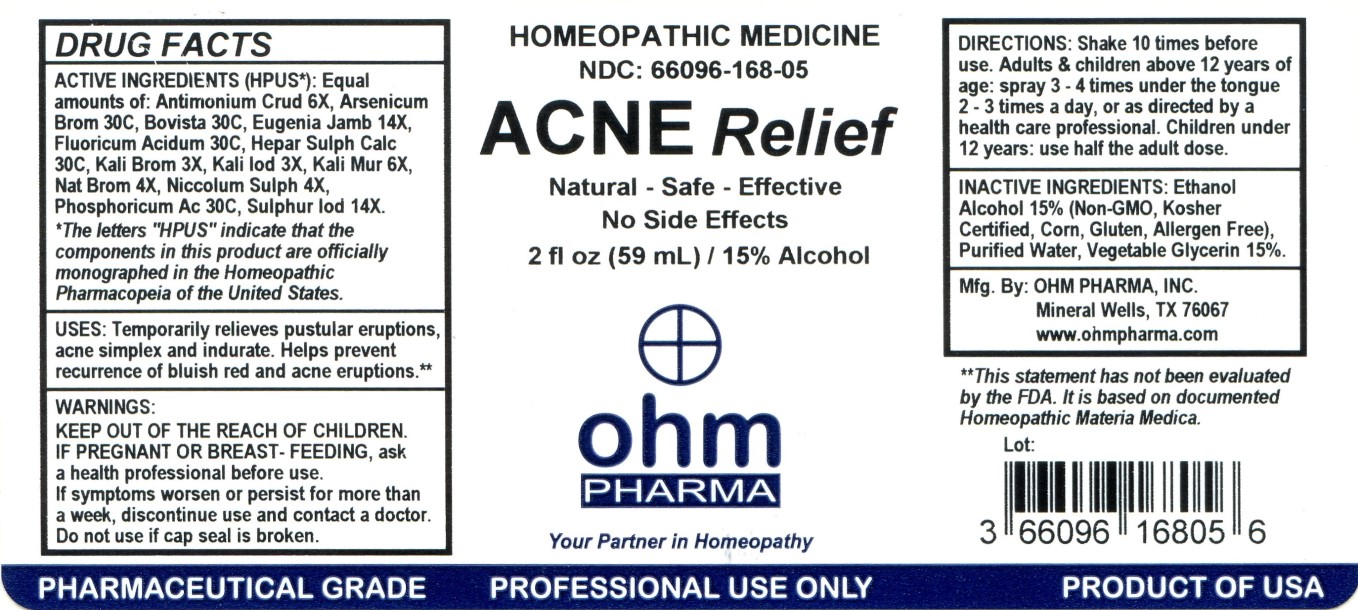 DRUG LABEL: Acne Relief
NDC: 66096-168 | Form: LIQUID
Manufacturer: OHM PHARMA INC.
Category: homeopathic | Type: HUMAN OTC DRUG LABEL
Date: 20211229

ACTIVE INGREDIENTS: ANTIMONY TRISULFIDE 6 [hp_X]/59 mL; ARSENIC TRIBROMIDE 30 [hp_C]/59 mL; LYCOPERDON UTRIFORME FRUITING BODY 30 [hp_C]/59 mL; SYZYGIUM JAMBOS SEED 14 [hp_X]/59 mL; HYDROFLUORIC ACID 30 [hp_C]/59 mL; CALCIUM SULFIDE 30 [hp_C]/59 mL; POTASSIUM BROMIDE 3 [hp_X]/59 mL; POTASSIUM IODIDE 3 [hp_X]/59 mL; POTASSIUM CHLORIDE 6 [hp_X]/59 mL; SODIUM BROMIDE 4 [hp_X]/59 mL; NICKEL SULFATE HEXAHYDRATE 4 [hp_X]/59 mL; PHOSPHORIC ACID 30 [hp_C]/59 mL; SULFUR IODIDE 14 [hp_X]/59 mL
INACTIVE INGREDIENTS: GLYCERIN; ALCOHOL; WATER

Acne Relief

ACTIVE INGREDIENT

ACTIVE INGREDIENTS (HPUS*): Equal amounts of: Antimonium Crud 6X, Arsenicum Brom 30C, Bovista 30C, Eugenia Jamb 14X, Fluoricum Acidum 30C, Hepar Sulph Calc 30C, Kali Brom 3X, Kali Iod 3X, Kali Mur 6X, Nat Brom 4X, Niccolum Sulph 4X, Phosphoricum Ac 30C, Sulphur Iod 14X.

*The letters "HPUS" indicate that the components in this product are officially monographed in the Homeopathic Pharmacopeia of the United States.

INDICATIONS AND USAGE

USES: Temporarily relieves pustular eruptions, acne simplex and indurate. Helps prevent recurrence of bluish red and acne eruptions.**

WARNINGS

WARNINGS: KEEP OUT OF THE REACH OF CHILDREN. IF PREGNANT OR BREAST - FEEDING, ask a health professional before use. If symptons worsen or persist for more than a week, discontinue use and contact a doctor. Do not use if cap seal is broken.

KEEP OUT OF THE REACH OF CHILDREN.

DOSAGE AND ADMINISTRATION

DIRECTIONS: Shake 10 times before use. Adults & children above 12 years of age: spray 3-4 times under the tongue 2-3 times a day, or as directed by a health care professional. Children under 12 years: use half the adult dose.

OTHER SAFETY INFORMATION

**This statement has not been evaluated by the FDA. It is based on documented Homeopathic Materia Medica.

INACTIVE INGREDIENT

INACTIVE INGREDIENTS: Ethanol Alcohol 15% (Non-GMO, Kosher Certified, Corn, Gluten, Allergen Free), Purified Water, Vegetable Glycerin 15%.

QUESTIONS

Mfg By: OHM Pharma, Inc. Mineral Wells, TX 76067

www.ohmpharma.com

PACKAGE LABEL

HOMEOPATHIC MEDICINE

NDC: 66096-168-05

ACNE RELIEF

Natural - Safe - Effective

No Side Effects

2 fl oz (59 ml) / 15% Alcohol

Your Partner In Homeopathy

PURPOSE

Acne Relief